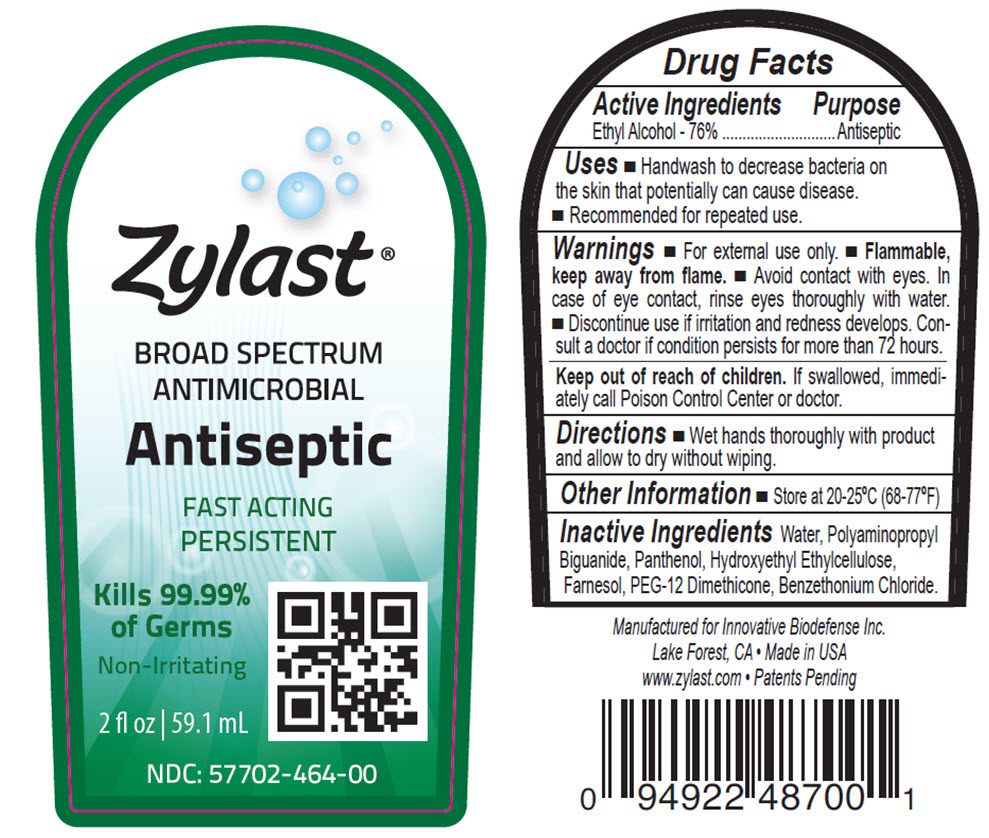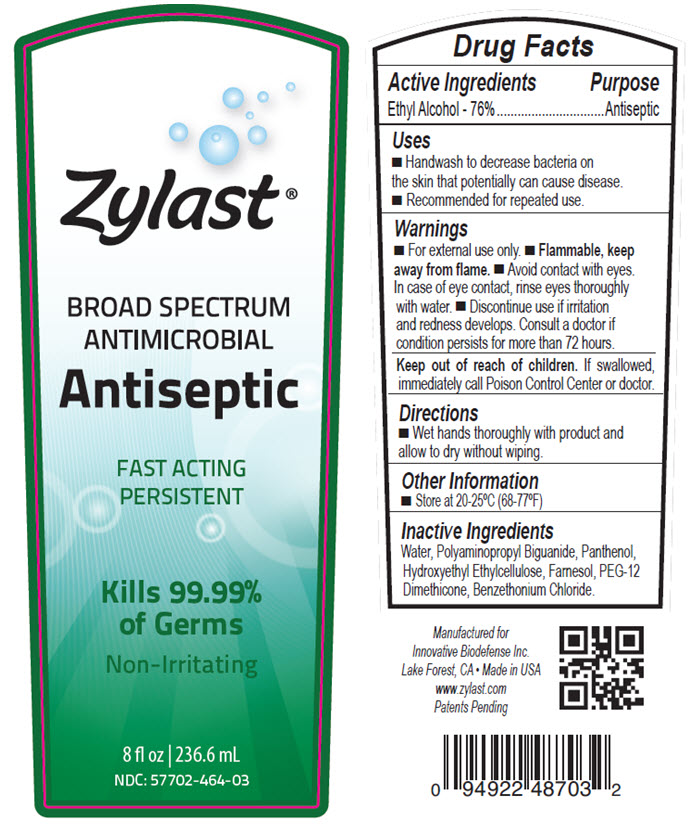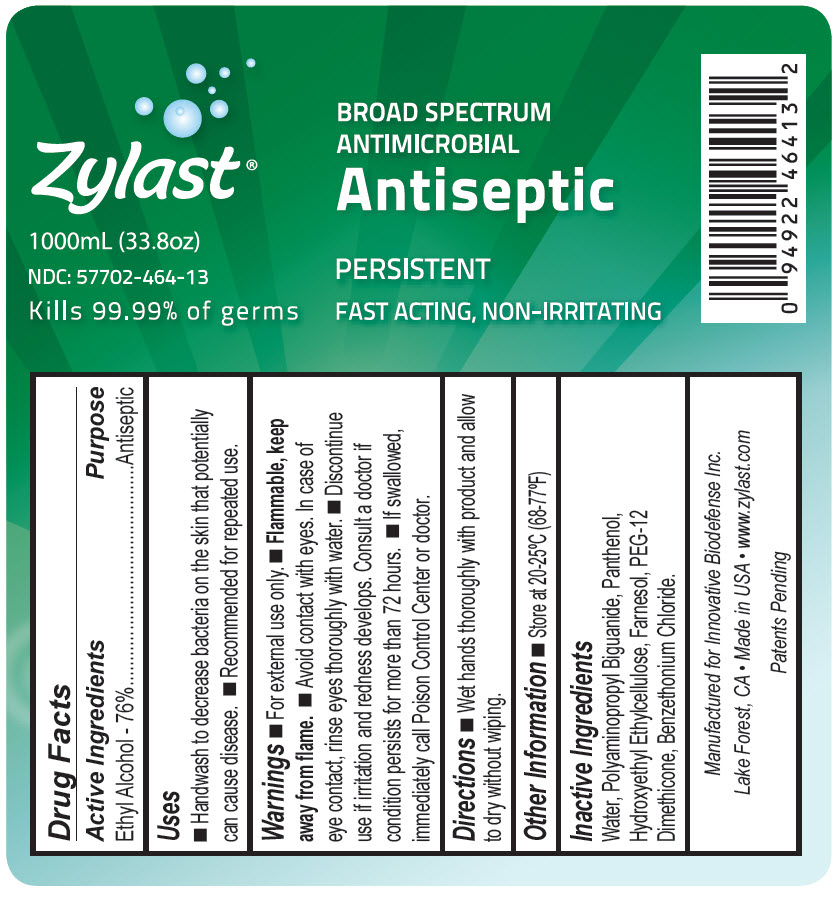 DRUG LABEL: Zylast Antiseptic
NDC: 57702-464 | Form: LIQUID
Manufacturer: Bocchi Laboratories Inc.
Category: otc | Type: HUMAN OTC DRUG LABEL
Date: 20140313

ACTIVE INGREDIENTS: ALCOHOL 0.76 mL/1 mL
INACTIVE INGREDIENTS: FARNESOL; WATER; POLIHEXANIDE; PANTHENOL; BENZETHONIUM CHLORIDE

Zylast Antiseptic
Drug Facts

Active Ingredients

Ethyl alcohol 76%

Purpose

Antiseptic

Uses

- Handwash to decrease bacteria on the skin that potentially can cause disease.
- Recommended for repeated use.

Warnings

- For external use only.
- Flammable. Keep away from flame.
- Discontinue use if irritation and redness develops. Consult a doctor if condition persists for more than 72 hours.

Keep out of reach of children.

If swallowed, immediately call Poison Control Center or doctor.

Directions

- Wet hands thoroughly with product and allow to dry without wiping.

Other Information

- Store at 20-25°C (68-77°F)

Inactive ingredients

Water, Polyaminopropyl Biguanide, Panthenol, Hydroxyethyl Ethylcellulose, Farnesol, PEG- 12 Dimethicone, Benzethonium Chloride.

Active Ingredients

Ethyl alcohol 76%

Purpose

Antiseptic

Uses

- Handwash to decrease bacteria on the skin that potentially can cause disease.
- Recommended for repeated use.

Warnings

- For external use only.
- Flammable, keepaway from flame.
- Avoid contact with eyes. In case of eye contact, rinse eyes thoroughly with water.
- Discontinue use if irritation and redness develops. Consult a doctor if condition persists for more than 72 hours.
- If swallowed, immediately call Poison Control Center or doctor.

Directions

- Wet hands thoroughly with product and allow to dry without wiping.

Other Information

- Store at 20-25°C (68-77°F)

Inactive Ingredients

Water, Polyaminopropyl Biguanide, Panthenol, Hydroxyethyl Ethylcellulose, Farnesol, PEG- 12 Dimethicone, Benzethonium Chloride.

Package/Label Principal Display Panel

NDC 57702-464-00
Zylast
Broad Spectrum
Antimicrobial
Antiseptic
2 fl oz/ 59.1 mL

Package/Label Principal Display Panel

NDC 57702-464-03
Zylast
Broad Spectrum
Antimicrobial
Antiseptic
8 fl oz 236.6 mL

Package/Label Principal Display Panel

NDC 57702-464-13
Zylast
Broad Spectrum
Antimicrobial
Antiseptic
1000mL (33.8oz)